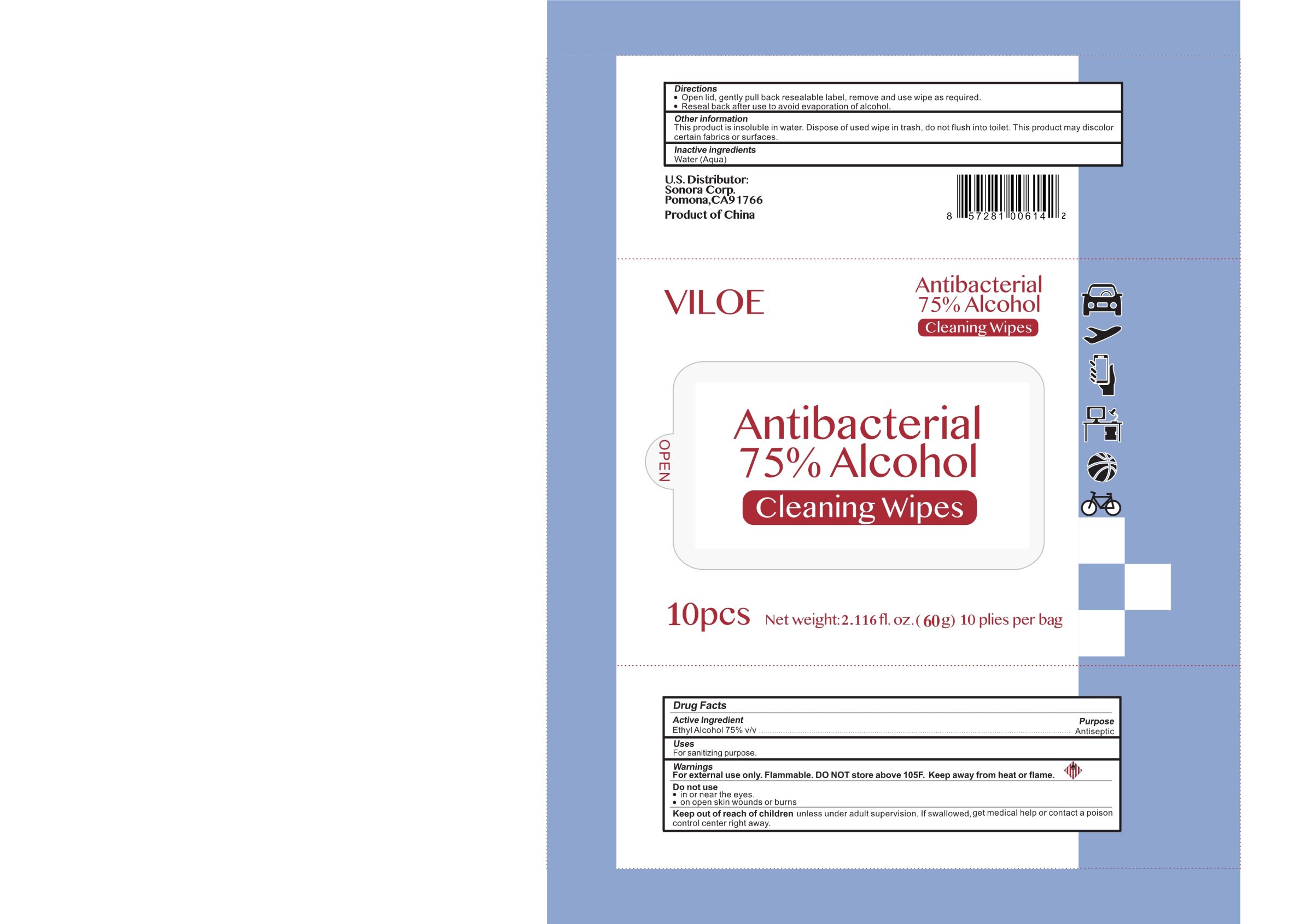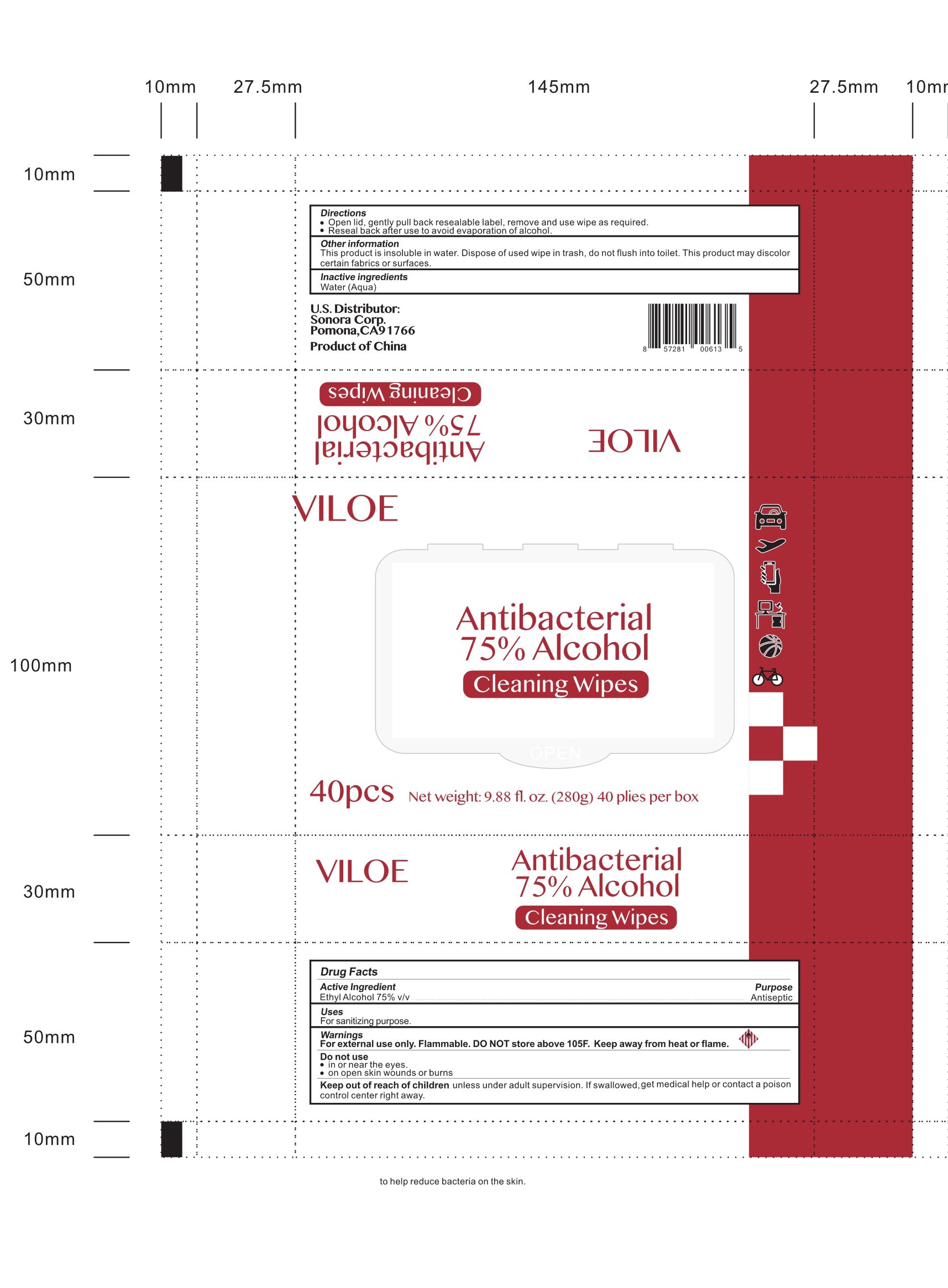 DRUG LABEL: VILOE Antibacterial 75% Alcohol Cleaning Wipes
NDC: 78733-020 | Form: CLOTH
Manufacturer: Sonora Corporation
Category: otc | Type: HUMAN OTC DRUG LABEL
Date: 20200812

ACTIVE INGREDIENTS: ALCOHOL 75 mL/100 mL
INACTIVE INGREDIENTS: WATER

VILOE Antibacterial 75% Alcohol Cleaning Wipes
10pcs 4ml 78733-020-01
40pcs 5ml 78733-020-02

Active Ingredient(s)

Ethyl Alcohol 75% v/v

Purpose

Antiseptic

Use

For sanitizing purpose.

Warnings

- For external use only.
- Flammable. DO NOT store above 105℉. Keep away from heat or flame.

Do not use

- in or near the eyes.
- on open skin wounds or burns.

Keep out of reach of children unless under adult supervision. If swallowed, get medical help or contact a poison control center right away.

Directions

- Open lid, gently pull back resealable label, remove and use wipe as required.
- Reseal back after use to avoid evaporation of alcohol.

Other information

This product is insoluble in water. Dispose of used wipe in trash, do not flush into toilet. This product may discolor certain fabrics or surfaces.

Inactive ingredients

Water(Aqua)

Package Label - Principal Display Panel

10pcs NDC: 78733-020-01

40pcs NDC: 78733-020-02